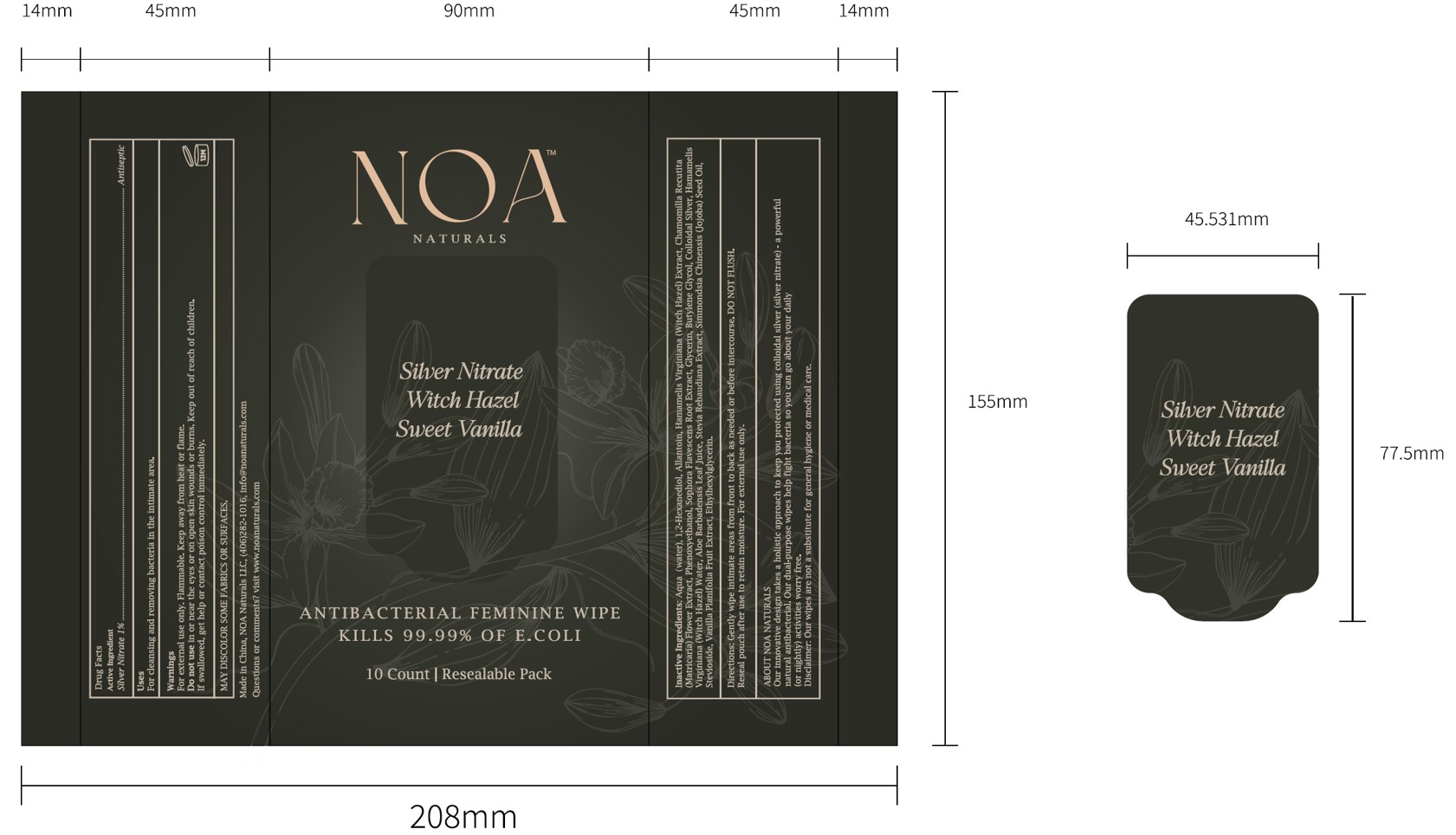 DRUG LABEL: ANTIBACTERIAL FEMININE WIPE
NDC: 84938-004 | Form: CLOTH
Manufacturer: Foshan Sugar Max Cosmetics CO.,Ltd
Category: otc | Type: HUMAN OTC DRUG LABEL
Date: 20251210

ACTIVE INGREDIENTS: SILVER NITRATE 0.01 g/1 1
INACTIVE INGREDIENTS: STEVIOSIDE; HAMAMELIS VIRGINIANA ROOT BARK/STEM BARK; ALLANTOIN; ETHYLHEXYLGLYCERIN; BUTYLENE GLYCOL; WATER; GLYCERIN; VANILLA PLANIFOLIA FRUIT; SIMMONDSIA CHINENSIS (JOJOBA) SEED OIL; PHENOXYETHANOL; 1,2-HEXANEDIOL; SOPHORA FLAVESCENS ROOT; ALOE VERA LEAF JUICE; STEVIA REBAUDIUNA LEAF; HAMAMELIS VIRGINIANA TOP WATER; MATRICARIA CHAMOMILLA ROOT

84938-004 ANTIBACTERIAL FEMININE WIPE

ACTIVE INGREDIENT

Silver Nitrate 1%

PURPOSE

Antiseptic

INDICATIONS AND USAGE

For cleansing and removing bacteria in the intimate area.

WARNINGS

For external use only.

Flammable.

Do not use in or near the eyes or on open skin wounds or burns

WHEN USING

Keep away from heat or flame

Keep out of reach of children.get help or contact poison control immediately.If swallowed,

DOSAGE AND ADMINISTRATION

Directions: Gently wipe intimate areas from front to back as needed or before intercourse. DO NOT FLUISH
Reseal pouch after use to retain moisture. For external use only.

INACTIVE INGREDIENT

Aqua (Water)
1,2‑Hexanediol
Allantoin
Hamamelis Virginiana (Witch Hazel) Extract
Chamomilla Recutita (Matricaria) Flower Extract
Phenoxyethanol
Sophora Flavescens Root Extract
Glycerin
Butylene Glycol
Hamamelis Virginiana (Witch Hazel) Water
Aloe Barbadensis Leaf Juice
Stevia Rebaudiana Extract
Simmondsia Chinensis (Jojoba) Seed Oil
Stevioside
Vanilla Planifolia Fruit Extract
Ethylhexylglycerin